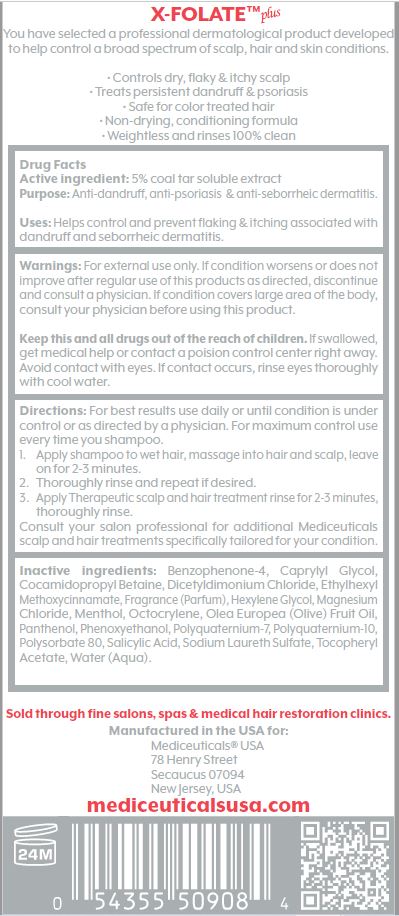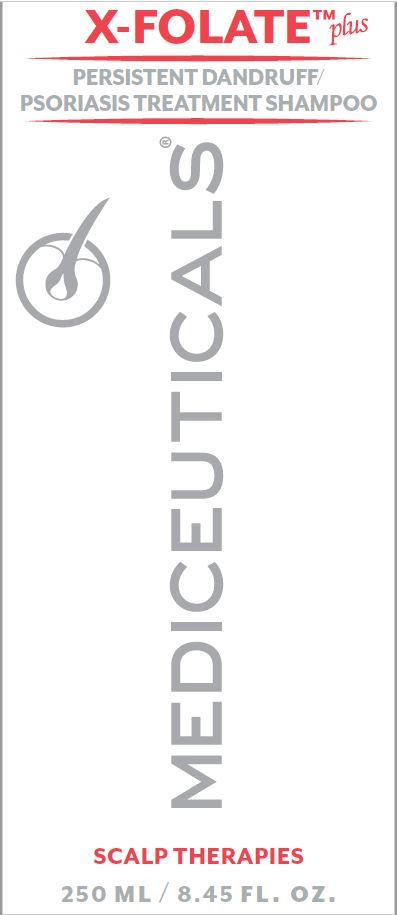 DRUG LABEL: X-FOLATE

NDC: 59279-516 | Form: SHAMPOO
Manufacturer: Mediceutical Laboratories, LTD
Category: otc | Type: HUMAN OTC DRUG LABEL
Date: 20220113

ACTIVE INGREDIENTS: COAL TAR 5 g/100 mL
INACTIVE INGREDIENTS: SULISOBENZONE; CAPRYLYL GLYCOL; COCAMIDOPROPYL BETAINE; DICETYLDIMONIUM CHLORIDE; OCTINOXATE; HEXYLENE GLYCOL; MAGNESIUM CHLORIDE; MENTHOL; OCTOCRYLENE; OLIVE OIL; PANTHENOL; PHENOXYETHANOL; POLYQUATERNIUM-7 (70/30 ACRYLAMIDE/DADMAC; 1600 KD); POLYQUATERNIUM-10 (1000 MPA.S AT 2%); POLYSORBATE 80; SALICYLIC ACID; SODIUM LAURETH SULFATE; .ALPHA.-TOCOPHEROL ACETATE; WATER

Mediceutical Laboratories - X-FOLATE PLUS (59279-516)

Active Ingredient

5% coal tar soluble extract

Purpose

anti-dandruff, anti-psoriasis, anti-seborrheic dermatitis

Uses

Helps control and prevent flaking & itching associated with dandruff and seborrheic dermatitis.

Warnings

For external use only. If condition worsens or does not improve after regular use of this products as directed, discontinue a nd consult a physician. If condition covers large area of the body, consult your physician before using this product.

KEEP OUT OF REACH OF CHILDREN

Keep this and all drugs out of the reach of children. If swallowed, get medical help or contact a poision control center right away. Avoid contact with eyes. If contact occurs, rinse eyes thoroughly with cool water.

Directions

For best results use daily or until condition is under control or as directed by a physician. For maximum control use every time you shampoo.

1. Apply shampoo to wet hair, massage into hair and scalp, leave on for 2-3 minutes.
2. Thoroughly rinse and repeat if desired.
3. Apply Therapeutic scalp and hair treatment rinse for 2-3 minutes, thoroughly rinse.

Consult your salon professional for additional Mediceuticals scalp and hair treatments specifically tailored for your condition.

Inactive Ingredients

Benzophenone-4, Caprylyl Glycol, Cocamidopropyl Betaine, Dicetyldimonium Chloride, Ethylhexyl Methoxycinnamate, Fragrance (Parfum), Hexylene Glycol, Magnesium Chloride, Menthol, Octocrylene, Olea Europea (Olive) Fruit Oil, Panthenol, Phenoxyethanol, Polyquaternium-7, Polyquaternium-10, Polysorbate 80, Salicylic Acid, Sodium Laureth Sulfate, Tocopheryl Acetate, Water (Aqua).